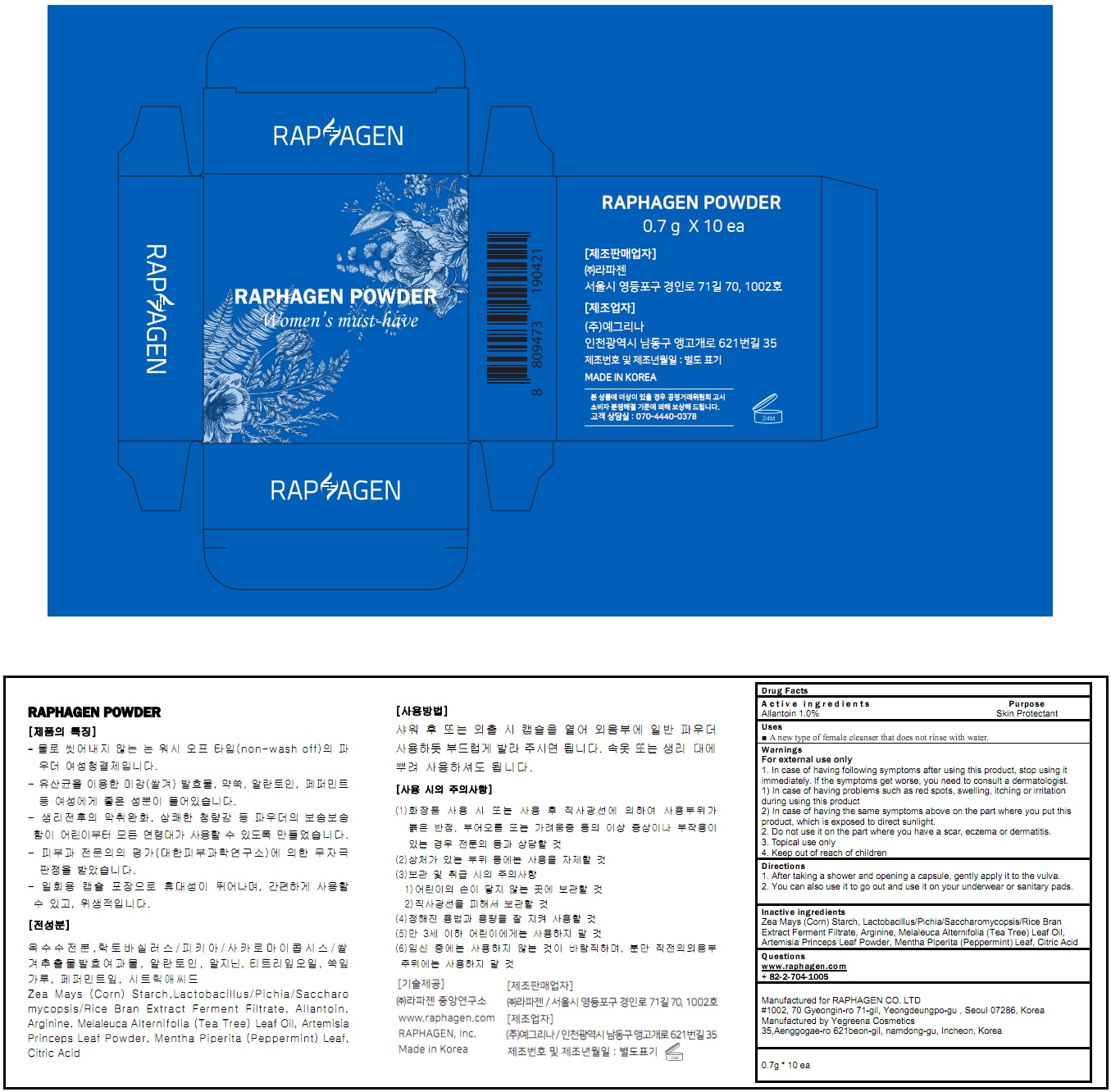 DRUG LABEL: RAPHAGEN
NDC: 71125-100 | Form: POWDER
Manufacturer: RAPHAGEN CO. LTD
Category: otc | Type: HUMAN OTC DRUG LABEL
Date: 20171120

ACTIVE INGREDIENTS: Allantoin 0.007 g/0.7 g
INACTIVE INGREDIENTS: STARCH, CORN; Arginine

ACTIVE INGREDIENT

Active ingredients: Allantoin 1.0%

INACTIVE INGREDIENT

Inactive ingredients: Zea Mays (Corn) Starch, Lactobacillus/Pichia/Saccharomycopsis/Rice Bran Extract Ferment Filtrate, Arginine, Melaleuca Alternifolia (Tea Tree) Leaf Oil, Artemisia Princeps Leaf Powder, Mentha Piperita (Peppermint) Leaf, Citric Acid

PURPOSE

Purpose: Skin Protectant

WARNINGS

Warnings: For external use only 1. In case of having following symptoms after using this product, stop using it immediately. If the symptoms get worse, you need to consult a dermatologist. 1) In case of having problems such as red spots, swelling, itching or irritation during using this product 2) In case of having the same symptoms above on the part where you put this product, which is exposed to direct sunlight. 2. Do not use it on the part where you have a scar, eczema or dermatitis. 3. Topical use only 4. Keep out of reach of children

KEEP OUT OF REACH OF CHILDREN

Uses

Uses: A new type of female cleanser that does not rinse with water.

Direction

1. After taking a shower and opening a capsule, gently apply it to the vulva. 2. You can also use it to go out and use it on your underwear or sanitary pads.

QUESTIONS

www.raphagen.com

+ 82-2-704-1005